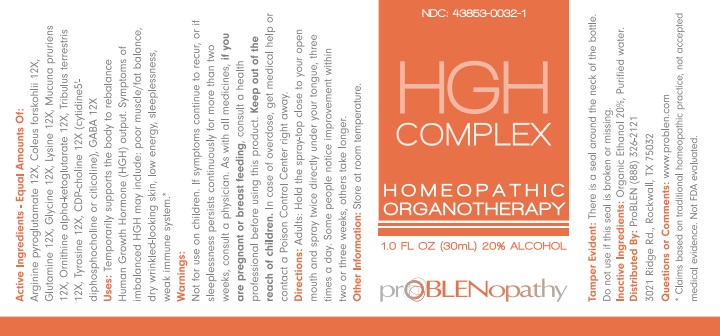 DRUG LABEL: HGH COMPLEX
NDC: 43853-0032 | Form: SPRAY
Manufacturer: ProBlen
Category: homeopathic | Type: HUMAN OTC DRUG LABEL
Date: 20221130

ACTIVE INGREDIENTS: ARGININE PIDOLATE 12 [hp_X]/30 mL; PLECTRANTHUS BARBATUS ROOT 12 [hp_X]/30 mL; GLUTAMINE 12 [hp_X]/30 mL; GLYCINE 12 [hp_X]/30 mL; LYSINE 12 [hp_X]/30 mL; MUCUNA PRURIENS SEED 12 [hp_X]/30 mL; DIORNITHINE OXOGLURATE 12 [hp_X]/30 mL; TRIBULUS TERRESTRIS WHOLE 12 [hp_X]/30 mL; TYROSINE 12 [hp_X]/30 mL; CITICOLINE 12 [hp_X]/30 mL; .GAMMA.-AMINOBUTYRIC ACID 12 [hp_X]/30 mL
INACTIVE INGREDIENTS: ALCOHOL; WATER

HGH Complex

Active Ingredients - Equal Amounts Of:

Arginine pyroglutamate 12X, Coleus forskohlii 12X, Glutamine 12X, Glycine 12X, Lysine 12X, Mucuna pruriens 12X, Ornithine alpha-ketoglutarate 12X, Tribulus terrestris 12X, Tyrosine 12X, CDP-choline 12X (cytidine5'-diphosphocholine or citicoline), GABA 12X

*Claims based on traditional homeopathic practice, not accepted medical evidence. Not FDA evaluated.

INDICATIONS AND USAGE

Uses: Temporarily supports the body to rebalance Human Growth Hormone (HGH) output. Symptoms of imbalanced HGH may include: poor muscle/ fat balance, dry wrinkled-looking skin, low energy, sleeplessness, weak immune system.*

Warnings:

Not for use on children. If symptoms continue to recur, or if sleeplessness persists continuously for more than two weeks, consult a physician. As with all medicines, if you are pregnant or breast feeding, consult a heatlh professional before using this product. Keep out of reach of children. In case of overdose, get medical or contact a Poison Control Center right away.

Keep out of reach of children.

DOSAGE AND ADMINISTRATION

Directions: Adults: Hold the spray-top close to your open mouth and spray twice directly under your tongue, three times a day. Some people notice improvement within two or three weeks, others take longer.

Other Information: Store at room temperature.

Tamper Evident: There is a seal around the neck of the bottle. Do not use if this seal is broken or missing.

Inactive Ingredients: Organic Ethanol 20%, Purified water.

QUESTIONS

Distributed By: ProBLEN (888) 326-2121

3021 Ridge Rd., Rockwall, TX 75032

Questions or Comments: www.problen.com

PACKAGE LABEL

NDC: 43853-0032-1

HGH COMPLEX

HOMEOPATHIC ORGANOTHERAPY

1.0 FL OZ (30mL) 20% ALCOHOL

prOBLENopathy

PURPOSE

Uses: Temporarily supports the body to rebalance Human Growth Hormone (HGH) output.